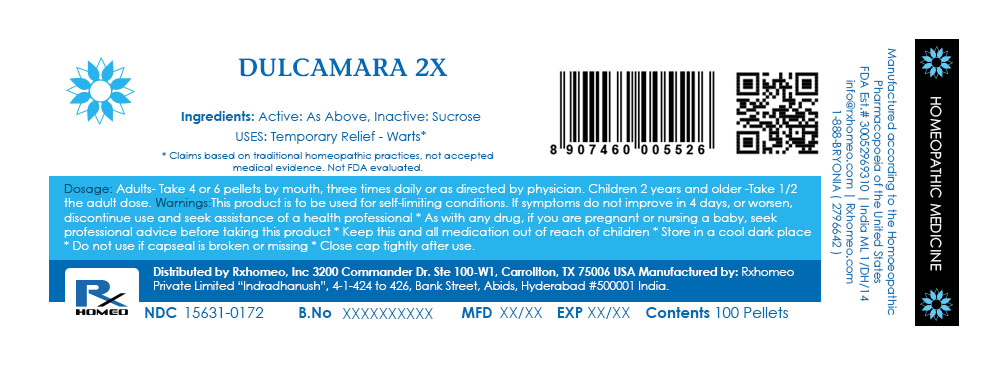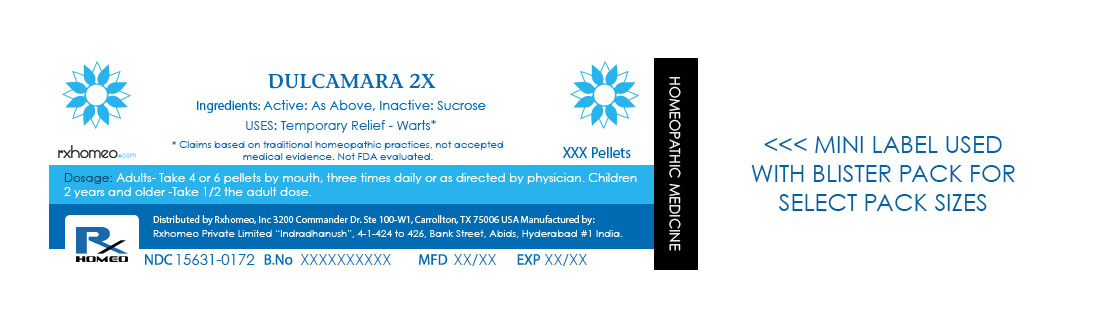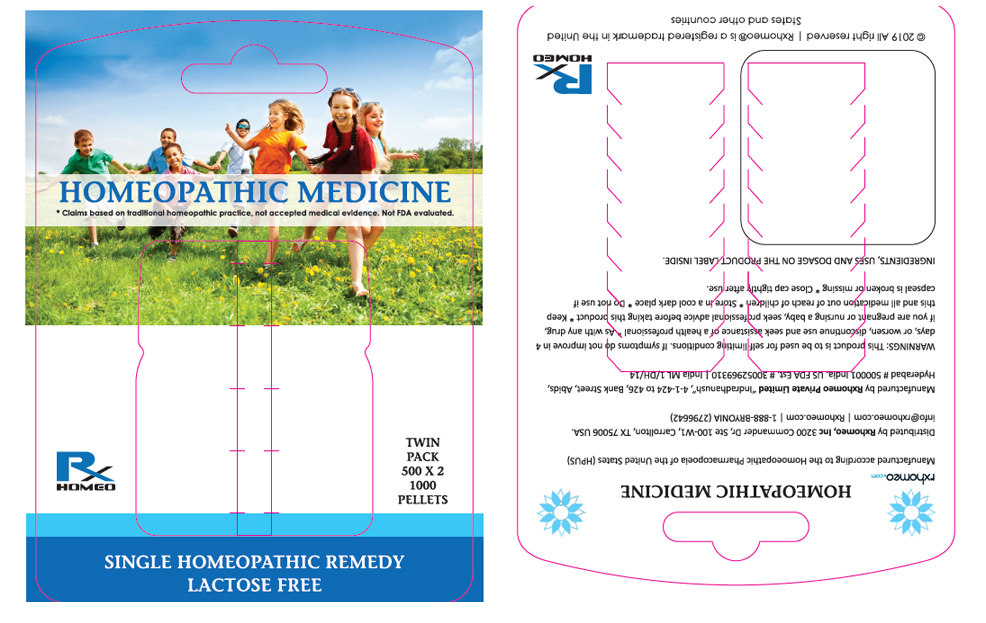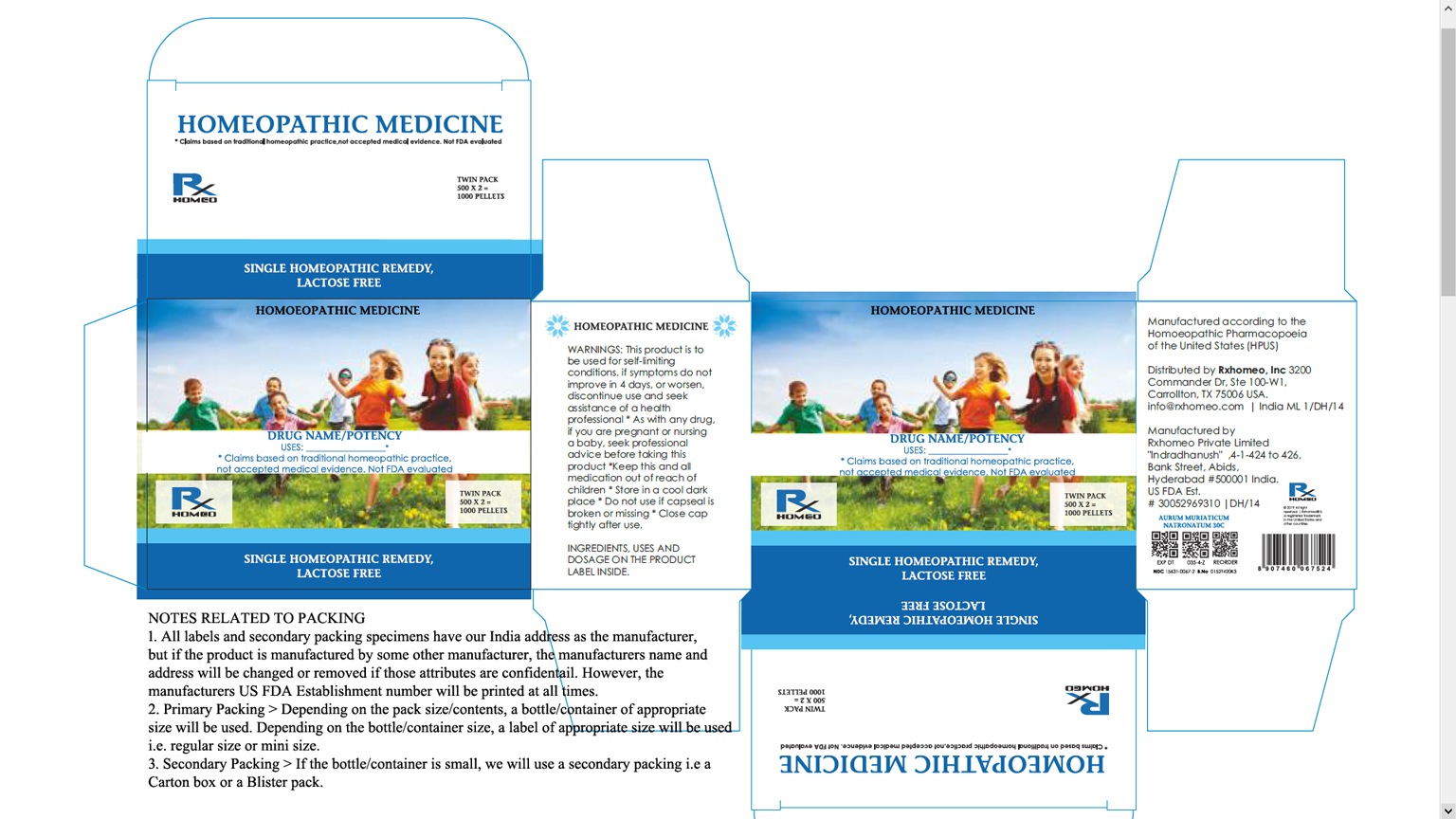 DRUG LABEL: DULCAMARA
NDC: 15631-0172 | Form: PELLET
Manufacturer: Rxhomeo Private Limited d.b.a. Rxhomeo, Inc
Category: homeopathic | Type: HUMAN OTC DRUG LABEL
Date: 20211023

ACTIVE INGREDIENTS: SOLANUM DULCAMARA TOP 2 [hp_X]/1 1
INACTIVE INGREDIENTS: SUCROSE

ACTIVE INGREDIENT

DULCAMARA HPUS 2X and higher

USES

USES: Temporary Relief - Warts*

* Claims based on traditional homeopathic practice, not accepted medical evidence. Not FDA evaluated.

INDICATIONS

Condition listed above or as directed by the physician

DOSAGE

Adults- Take 4 or 6 Pellets by mouth, three times daily or as suggested by physician. Children 2 years and older- take 1/2 the adult dose.

WARNINGS

This product is to be used for self-limiting conditions

STOP USE

If symptoms do not improve in 4 days, or worsen, discontinue use and seek assistance of health professional

PREGNANCY OR BREAST FEEDING

As with any drug, if you are pregnant, or nursing a baby, seek professional advice before taking this product

KEEP OUT OF REACH OF CHILDREN

Keep this and all medication out of reach of children

Do not use if capseal is broken or missing.

Close the cap tightly after use.

INACTIVE INGREDIENTS

Sucrose

STORAGE

Store in a cool dark place

QUESTIONS OR COMMENTS

www.Rxhomeo.com | 1.888.2796642 | info@rxhomeo.com

Rxhomeo, Inc 3200 Commander Dr, Ste 100-W1, Carrollton, TX 75006 USA